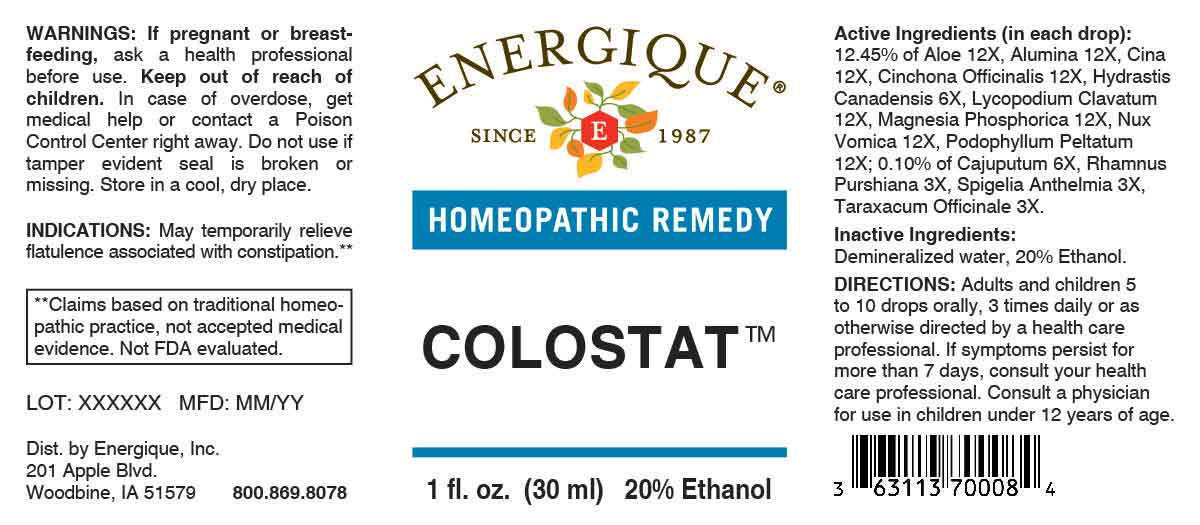 DRUG LABEL: Colostat
NDC: 44911-0901 | Form: LIQUID
Manufacturer: Energique, Inc.
Category: homeopathic | Type: HUMAN OTC DRUG LABEL
Date: 20260106

ACTIVE INGREDIENTS: RHODODENDRON TOMENTOSUM LEAFY TWIG 3 [hp_X]/1 mL; SPIGELIA ANTHELMIA WHOLE 3 [hp_X]/1 mL; TARAXACUM OFFICINALE 3 [hp_X]/1 mL; CAJUPUT OIL 6 [hp_X]/1 mL; GOLDENSEAL 6 [hp_X]/1 mL; ALOE 12 [hp_X]/1 mL; ALUMINUM OXIDE 12 [hp_X]/1 mL; ARTEMISIA CINA PRE-FLOWERING TOP 12 [hp_X]/1 mL; CINCHONA OFFICINALIS BARK 12 [hp_X]/1 mL; LYCOPODIUM CLAVATUM SPORE 12 [hp_X]/1 mL; MAGNESIUM PHOSPHATE, DIBASIC TRIHYDRATE 12 [hp_X]/1 mL; STRYCHNOS NUX-VOMICA SEED 12 [hp_X]/1 mL; PODOPHYLLUM 12 [hp_X]/1 mL
INACTIVE INGREDIENTS: WATER; ALCOHOL

DRUG FACTS:

ACTIVE INGREDIENTS:

(in each drop): 12.45% of Aloe 12X, Alumina 12X, Cina 12X, Cinchona Officinalis 12X, Hydrastis Canadensis 6X, Lycopodium Clavatum 12X, Magnesia Phosphorica 12X, Nux Vomica 12X, Podophyllum Peltatum 12X; 0.10% of Cajuputum 6X, Rhamnus Purshiana 3X, Spigelia Anthelmia 3X, Taraxacum Officinale 3X.

PURPOSE:

May temporarily relieve flatulence associated with constipation.**

**Claims based on traditional homeopathic practice, not accepted medical evidence. Not FDA evaluated.

WARNINGS:

If pregnant or breast-feeding, ask a health professional before use.

Keep out of reach of children. In case of overdose, get medical help or contact a Poison Control Center right away.

Do not use if tamper evident seal is broken or missing. Store in a cool, dry place.

KEEP OUT OF REACH OF CHILDREN:

In case of overdose, get medical help or contact a Poison Control Center right away.

DIRECTIONS:

Adults and children 5 to 10 drops orally, 3 times daily or as otherwise directed by a health care professional. If symptoms persist for more than 7 days, consult your health care professional. Consult a physician for use in children under 12 years of age.

INDICATIONS:

May temporarily relieve flatulence associated with constipation.**

**Claims based on traditional homeopathic practice, not accepted medical evidence. Not FDA evaluated.

INACTIVE INGREDIENTS:

Demineralized water, 20% Ethanol.

QUESTIONS:

Dist. by Energique, Inc.
201 Apple Blvd
Woodbine, IA 51579

800.869.8078

PACKAGE LABEL DISPLAY:

ENERGIQUE
SINCE 1987
HOMEOPATHIC REMEDY
COLOSTAT
1 fl. oz. (30 ml)